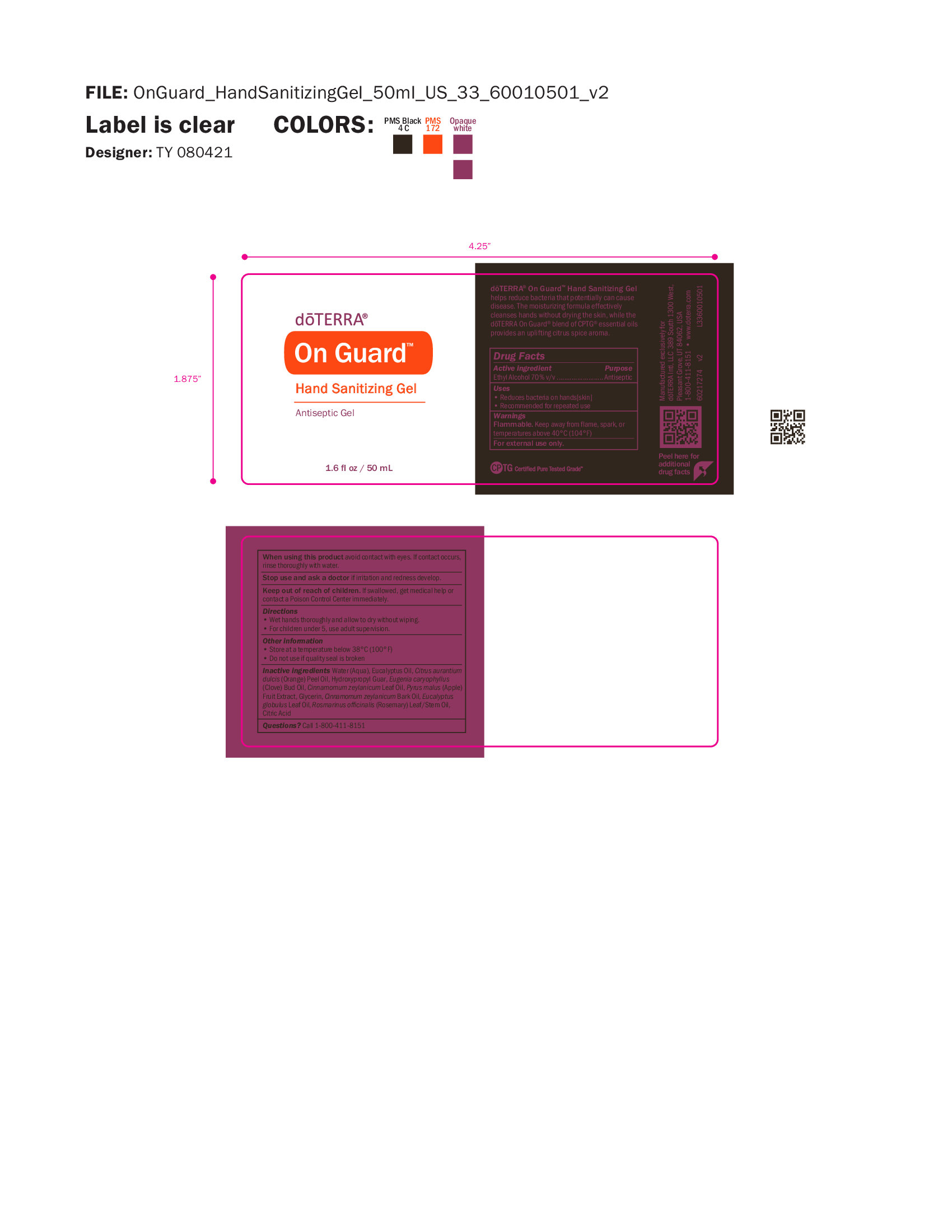 DRUG LABEL: On Guard Sanitizing Gel
NDC: 71630-098 | Form: GEL
Manufacturer: doTERRA International, LLC
Category: otc | Type: HUMAN OTC DRUG LABEL
Date: 20250128

ACTIVE INGREDIENTS: ALCOHOL 70 mL/100 mL
INACTIVE INGREDIENTS: WATER; EUCALYPTUS OIL; ORANGE OIL; HYDROXYPROPYL GUAR (2500-4500 MPA.S AT 1%); CLOVE OIL; CINNAMON LEAF OIL; GLYCERIN; CINNAMON BARK OIL; HYDRATED SILICA; BORON; EUCALYPTUS GLOBULUS LEAF; ROSEMARY OIL

On Guard Sanitizing Gel

Active ingredient Purpose
Ethyl Alcohol 70% v/v ......................... Antiseptic

Antiseptic, Hand Sanitizer

Uses

• Reduces bacteria on hands[skin]
• Recommended for repeated use

Warnings

Flammable. Keep away from flame, spark, or
temperatures above 40°C (104°F)
For external use only.

When using this product avoid contact with eyes. If contact occurs,
rinse thoroughly with water.

Stop use and ask a doctor if irritation and redness develop.

Keep out of reach of children. If swallowed, get medical help or
contact a Poison Control Center immediately.

Directions

• Wet hands thoroughly and allow to dry without wiping.
• For children under 5, use adult supervision.

Other information
• Store at a temperature below 38°C (100°F)
• Do not use if quality seal is broken

Inactive ingredients Water (Aqua), Eucalyptus Oil, Citrus aurantium
dulcis (Orange) Peel Oil, Hydroxypropyl Guar, Eugenia caryophyllus
(Clove) Bud Oil, Cinnamomum zeylanicum Leaf Oil, Pyrus malus (Apple)
Fruit Extract, Glycerin, Cinnamomum zeylanicum Bark Oil, Eucalyptus
globulus Leaf Oil, Rosmarinus officinalis (Rosemary) Leaf/Stem Oil,
Citric Acid

Questions? Call 1-800-411-8151

Primary Label